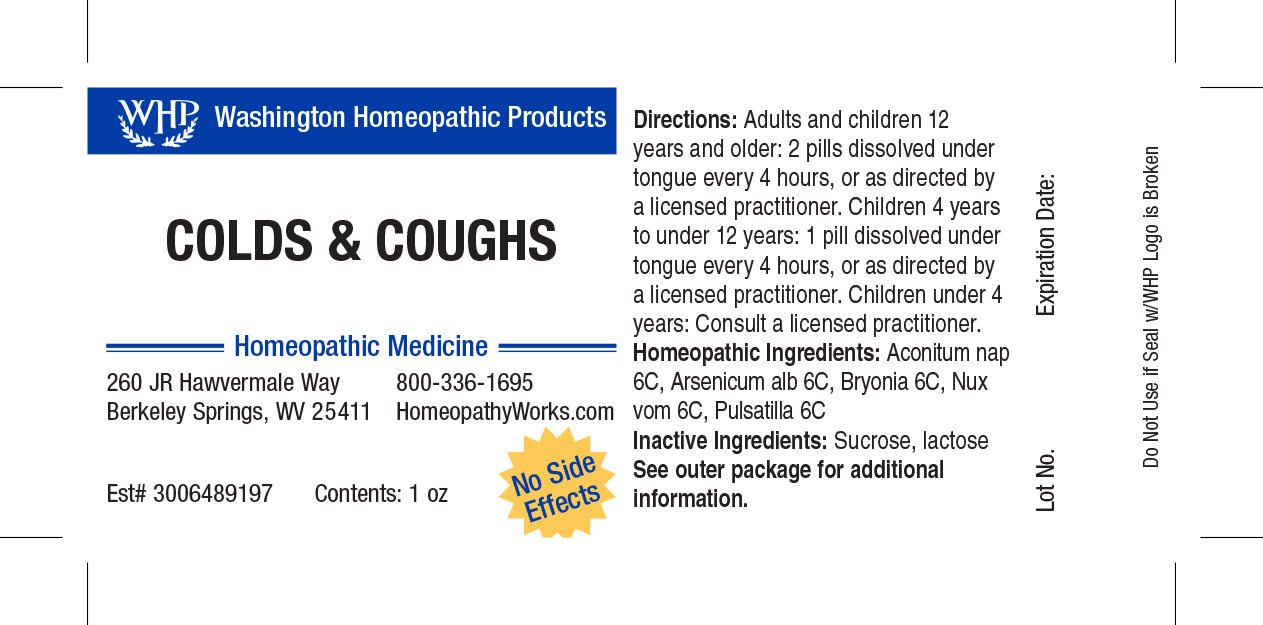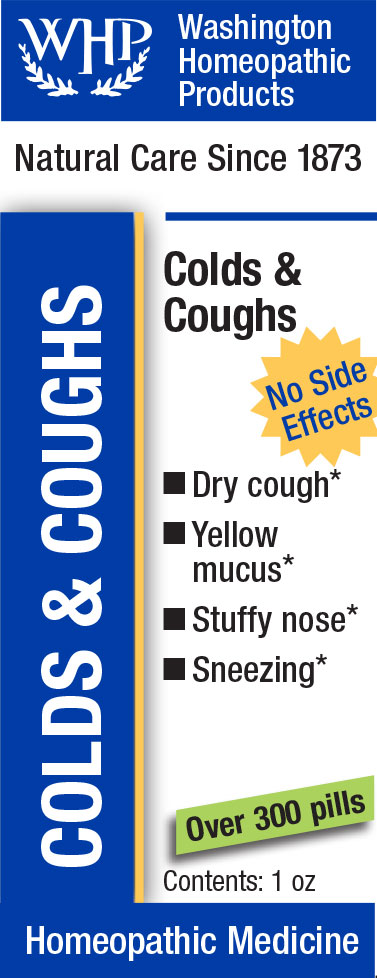 DRUG LABEL: WHP Colds and Cough
NDC: 71919-800 | Form: PELLET
Manufacturer: Washington Homeopathic Products
Category: homeopathic | Type: HUMAN OTC DRUG LABEL
Date: 20250128

ACTIVE INGREDIENTS: BRYONIA ALBA ROOT 6 [hp_C]/1 1; PULSATILLA VULGARIS 6 [hp_C]/1 1; ACONITUM NAPELLUS 6 [hp_C]/1 1; ARSENIC TRIOXIDE 6 [hp_C]/1 1; STRYCHNOS NUX-VOMICA SEED 6 [hp_C]/1 1
INACTIVE INGREDIENTS: SUCROSE; LACTOSE

WHP Colds & Cough

Active Ingredients

ACONITUM NAP 6C

BRYONIA 6C

PULSATILLA 6C

NUX VOM 6C

ARSENICUM ALB 6C

USES

Temporarily relieves dry hacking coughs due to colds.

KEEP OUT OF REACH OF CHILDREN

As with all medications, keep out of reach of children.

INDICATIONS

ACONITUM NAP Fear

BRYONIA Worse motion

PULSATILLA Weeping

NUX VOM Vomiting

ARSENICUM ALB Vomiting

STOP USE AND ASK DOCTOR

If symptoms persist or recur, discontinue use. If pregnant or nursing, consult a licensed practitioner before using this product.

DIRECTIONS

Directions: Adults and children 12 years and older: 2 pills dissolved under tongue every 4 hours, or as directed by a licensed practitioner. Children 4 years to under 12 years: 1 pill dissolved under tongue every 4 hours, or as directed by a licensed practitioner. Children under 4 years: Consult a licensed practitioner.

INACTIVE INGREDIENTS

Sucrose/Lactose